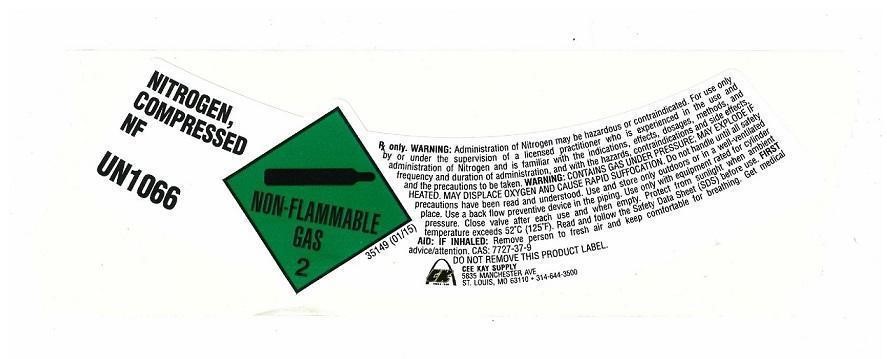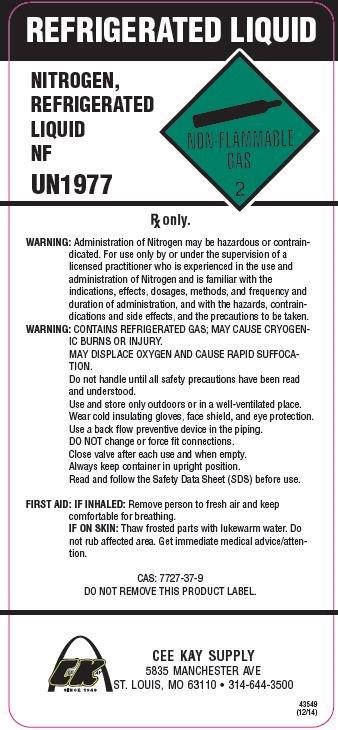 DRUG LABEL: NITROGEN
NDC: 10218-102 | Form: GAS
Manufacturer: CEE-KAY SUPPLY, INC.
Category: prescription | Type: HUMAN PRESCRIPTION DRUG LABEL
Date: 20260225

ACTIVE INGREDIENTS: NITROGEN 995 mL/1 L

Nitrogen

PACKAGE LABEL

NITROGEN, COMPRESSED NF
UN 1066
NON-FLAMMABLE GAS 2
Rx only. WARNING: Administration of Nitrogen may be hazardous or contraindicated. For use only by or under the supervision of a licensed practitioner who is experienced in the use and administration of Nitrogen and is familiar with the indications, effects, dosages, methods, and frequency and duration of administration, and with the hazards, contraindications, and side effects and the precautions to be taken. WARNING: CONTAINS GAS UNDER PRESSURE; MAY EXPLODE IF HEATED. MAY DISPLACE OXYGEN AND CAUSE RAPID SUFFOCATION. Do not handle until all safety precautions have been read and understood. Use and store only outdoors or in a well-ventilated place. Use a back flow preventive device in the piping. Use only with equipment rated for cylinder pressure. Close valve after each use and when empty. Proteve from sunlight when ambient temperature exceeds 52 degrees C (125 degrees F). Read and follow the Safety Data Sheet (SDS) before use. FIRST AID: IF INHALED: Remove person to fresh air and keep comfortable for breathing.Get medical advice/attention.
CAS: 7727-37-9
DO NOT REMOVE THIS PRODUCT LABEL.

CEE KAY SUPPLY

5835 MANCHESTER AVE

ST. LOUIS, MO 63110 . 314-644-3500

PACKAGE LABEL

REFRIGERATED LIQUID
NITROGEN, REFRIGERATED LIQUID NF
UN1977
NON-FLAMMABLE GAS 2
Rx only.
WARNING: Administration of Nitrogen may be hazardous or contraindicated. For use only by or under the supervision of a licensed practitioner who is experienced in the use and administration of Nitrogen and is familiar with the indications, effects, dosages, methods, and frequency and duration of administration, and with the hazards, contraindications and side effects, and the precautions to be taken.
WARNING: CONTAINS REFRIGERATED GAS; MAY CAUSE CRYOGENIC BURNS OR INJURY. MAY DISPLACE OXYGEN AND CAUSE RAPID SUFFOCATION. Do not handle until all safety precautions have been read and understood. Use and store only outdoors or in a well-ventilated place. Wear cold insulating gloves, face shield, and eye protection. Use a back flow preventive device in the piping. DO NOT change or force fit connections. Close valve after each use and when empty. Always keep container in upright position. Read and follow the Safety Data Sheet (SDS) before use.
FIRST AID: IF INHALED: Remove person to fresh air and keep comfortable for breathing. IF ON SKIN: Thaw frosted parts with lukewarm water. Do not rub affected area. Get immediate medical advice/attention.
CAS: 7727-37-9
DO NOT REMOVE THIS PRODUCT LABEL
CEE KAY SUPPLY
5835 MANCHESTER AVE
ST LOUIS, MO 63110
314-644-3500